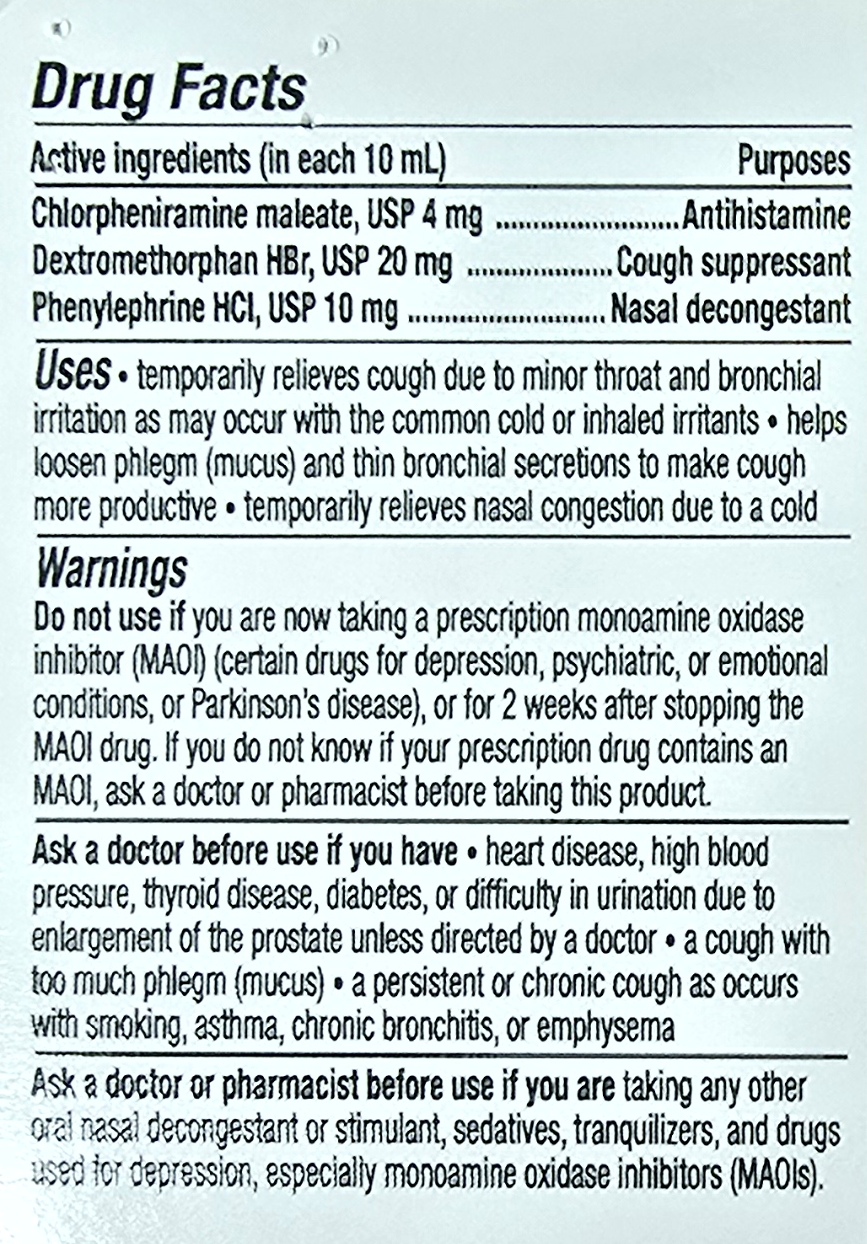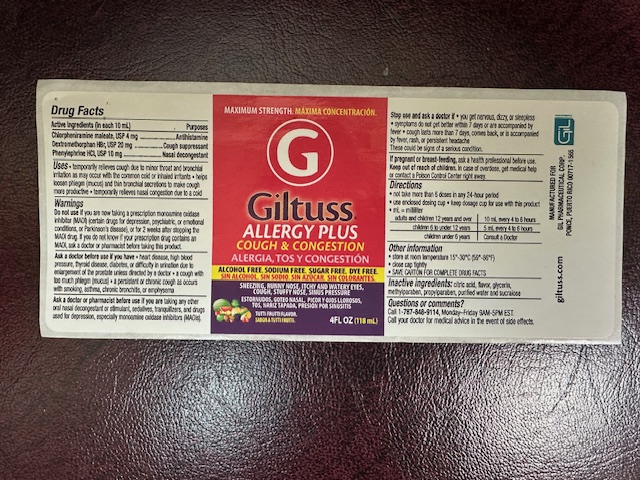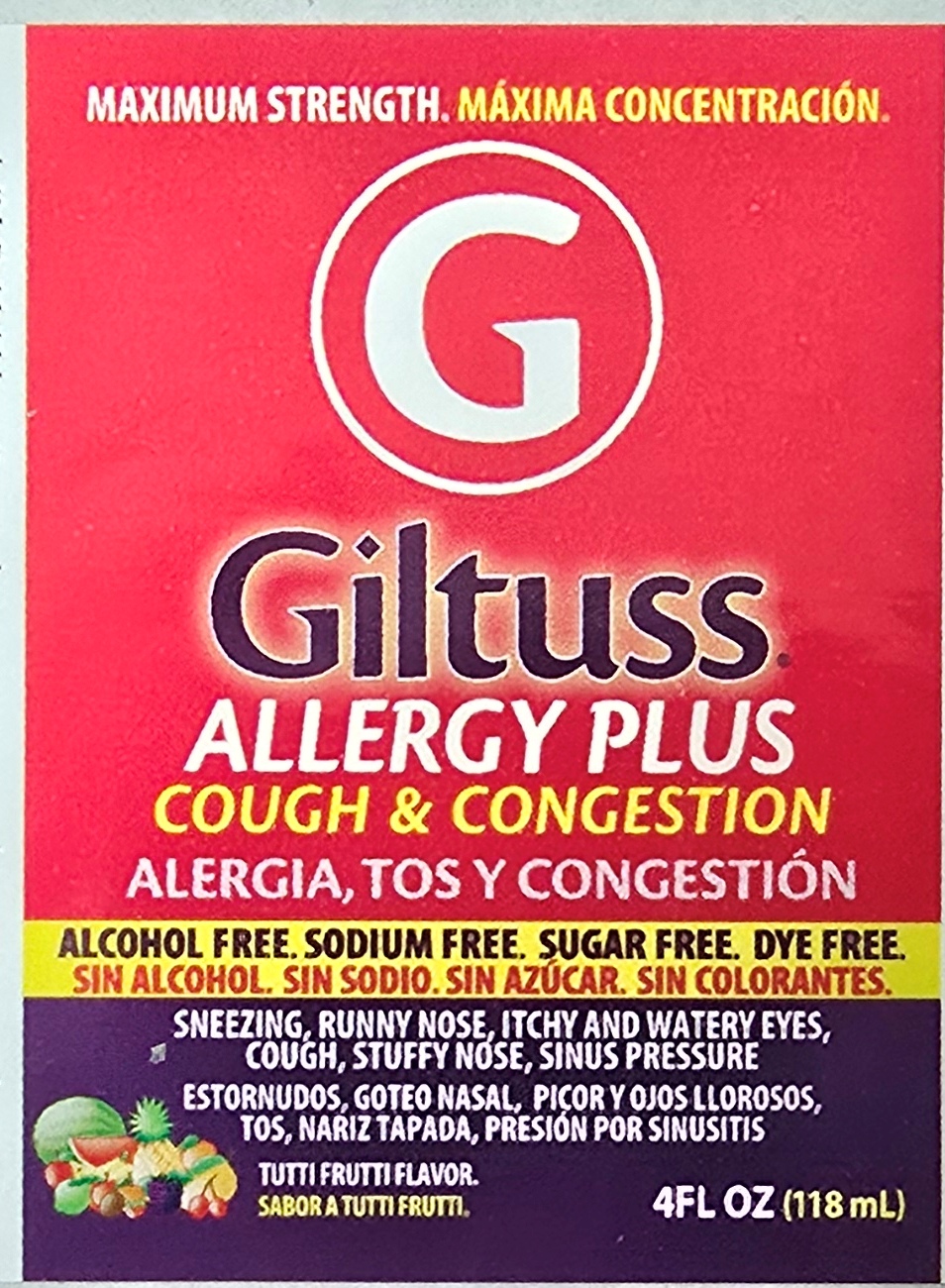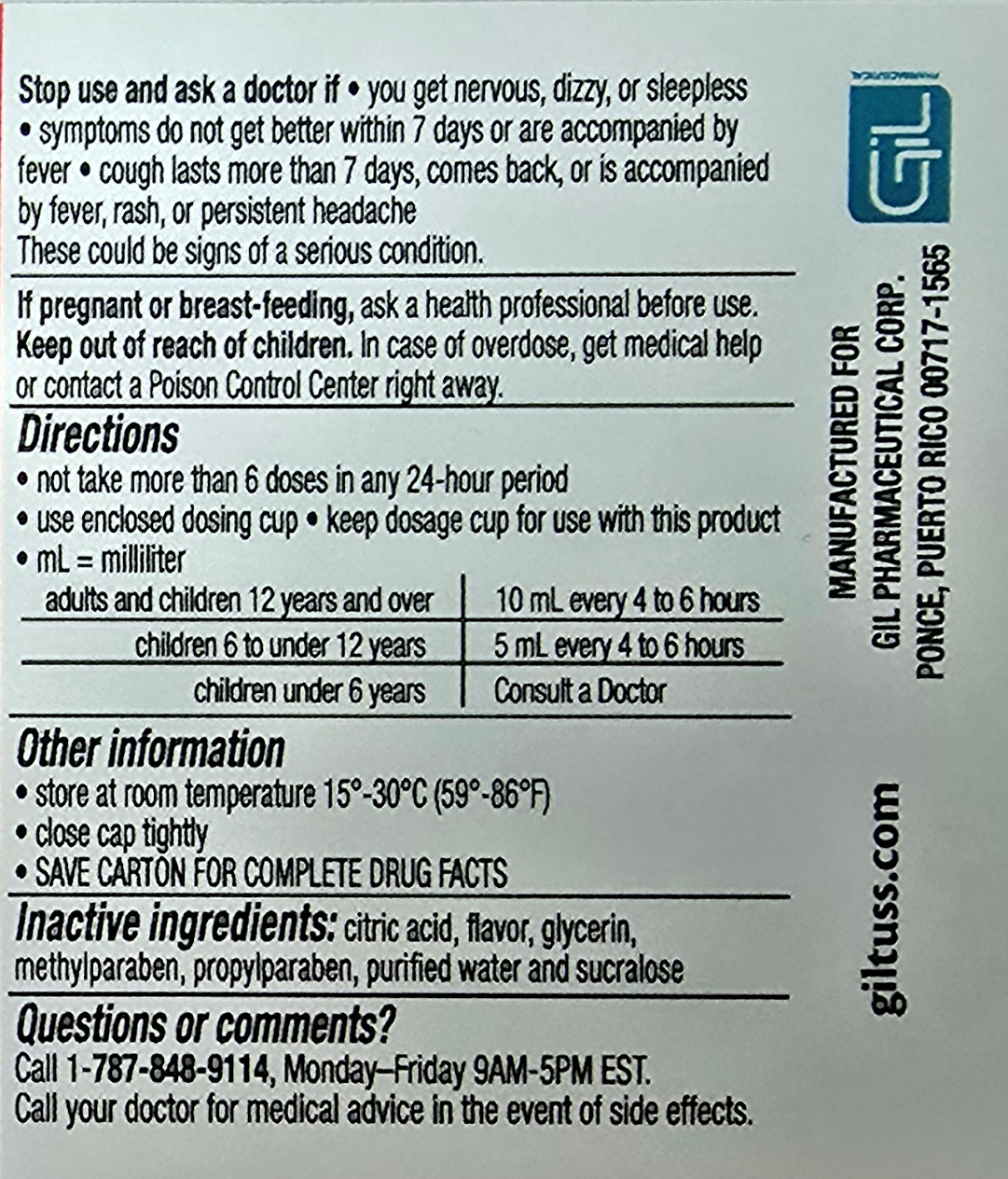 DRUG LABEL: Giltuss Allergy Plus
NDC: 65852-017 | Form: SOLUTION
Manufacturer: Dextrum Laboratories Inc.
Category: otc | Type: HUMAN OTC DRUG LABEL
Date: 20250925

ACTIVE INGREDIENTS: DEXTROMETHORPHAN HYDROBROMIDE 20 mg/10 mL; PHENYLEPHRINE HYDROCHLORIDE 10 mg/10 mL; CHLORPHENIRAMINE MALEATE 4 mg/10 mL
INACTIVE INGREDIENTS: WATER; SUCRALOSE; PROPYLPARABEN; CITRIC ACID; METHYLPARABEN; GLYCERIN

Giltuss Allergy Plus Cough & Congestion

Active ingredients

Active ingredients (in each 10 m) Purposes

Chlorpheniramine maleate, USP 4 mg -------------------------------Antihistamine

Dextromethorphan HBr, USP 20 mg -----------------------------------Cough supressant

Phenylephrine HCl, USP 10 mg -----------------------------------------Nasal descongestant

Uses

Temporary relieves:

Cough due to minor throat and bronchial irritation associated with the common cold or inhaled irritants, helps loosen phlegm (mucus) and thin bronchial secretions to make cough more productive, temporary relieves nasal congestion due to a cold

Warnings

Do not use

If your child is now taking a prescription monoamine oxidase inhibitor (MAOI) (certain drugs for depression, psychiatric, or emotional conditions, or Parkinson's disease), or for 2 weeks after stopping the MAOI drug. If you don’t know is your prescription drug contains and MAOI, ask a doctor or pharmacist before taking this product.

Ask a doctor before use if you have:

heart disease, high blood pressure, thyroid disease, diabetes, or difficulty in urination due to an enlarged prostate unless directed by a doctor, a cough with too much phlegm (mucus), a persistent or chronic cough as occurs with smoking, asthma, chronic bronchitis, or emphysema

Ak a doctor or pharmacist before use it

As a doctor or pharmacist before use if you ar etaking any other oral nasal descongestant or stimulant, sedatives, tranquilizer, and drugs used for depression, especially momoamine oxidase inhibitors (MAOI)

Stop use and ask a doctor if

if you get nervous, dizzy, or sleepless, symptoms do not get better within 7 days or are accompanied by fever, cough lasts more than 7 days, comeback, or is accompanied by fever,rash, or persistent headache

These could be signs of a serious condition.

If pregnant or breast- feeding, ask a health professional before use. Keep out of reach of children. In case of accidental overdose, get medical or professional help or contact a Poisson Control center immediately

Directions

Do not take more than 6 doses in any 24 hours period

use enclosed dosing cup

Keep dosage cup for use with this product

ml= milliliters

Adults and children 12 years & over 10 ml every 4 to 6 hours

Children 6 to under 12 years of age 5 ml every 4 to 6 hours

Children under 6 years of age Consult a doctor

hildren under 6 years of age Consult a doctor

Other information

Store at room temperature 15-30 °C (59° -86 ° F)
Close cap tightly
SAVE CARTON FOR COMPLETE DRUG FACTS

Inactive Ingredients

Citric Acid, flavor, glycerin, methylparaben, propylparaben, purified water and sucralose

Questions or comments?

Call 1-787-848-9114, Monday-Friday 9AM – 5PM EST

Call your doctor for medical advice in the event of side effects.

Indication and usage section

Do not take more than 6 doses in any 24 hours period

use enclosed dosing cup

Keep dosage cup for use with this product

ml= milliliters

Adults and children 12 years & over 10 ml every 4 to 6 hours

Children 6 to under 12 years of age 5 ml every 4 to 6 hours

Children under 6 years of age Consult a doctor

keep out of reach of children section

. In case of accidental overdose, get medical or professional help or contact a Poisson Control center immediately

PACKAGE LABEL

Maximum strength

Giltuss Allergy Plus

Cough & Congestion

Alcohol free, Sodium free, sugar free, dye free

Sneezing, runny nose, itchy and watery eyes, cough, stuffy nose, sinus pressure

Tutti Frutti flavor

4 floz 118 ml